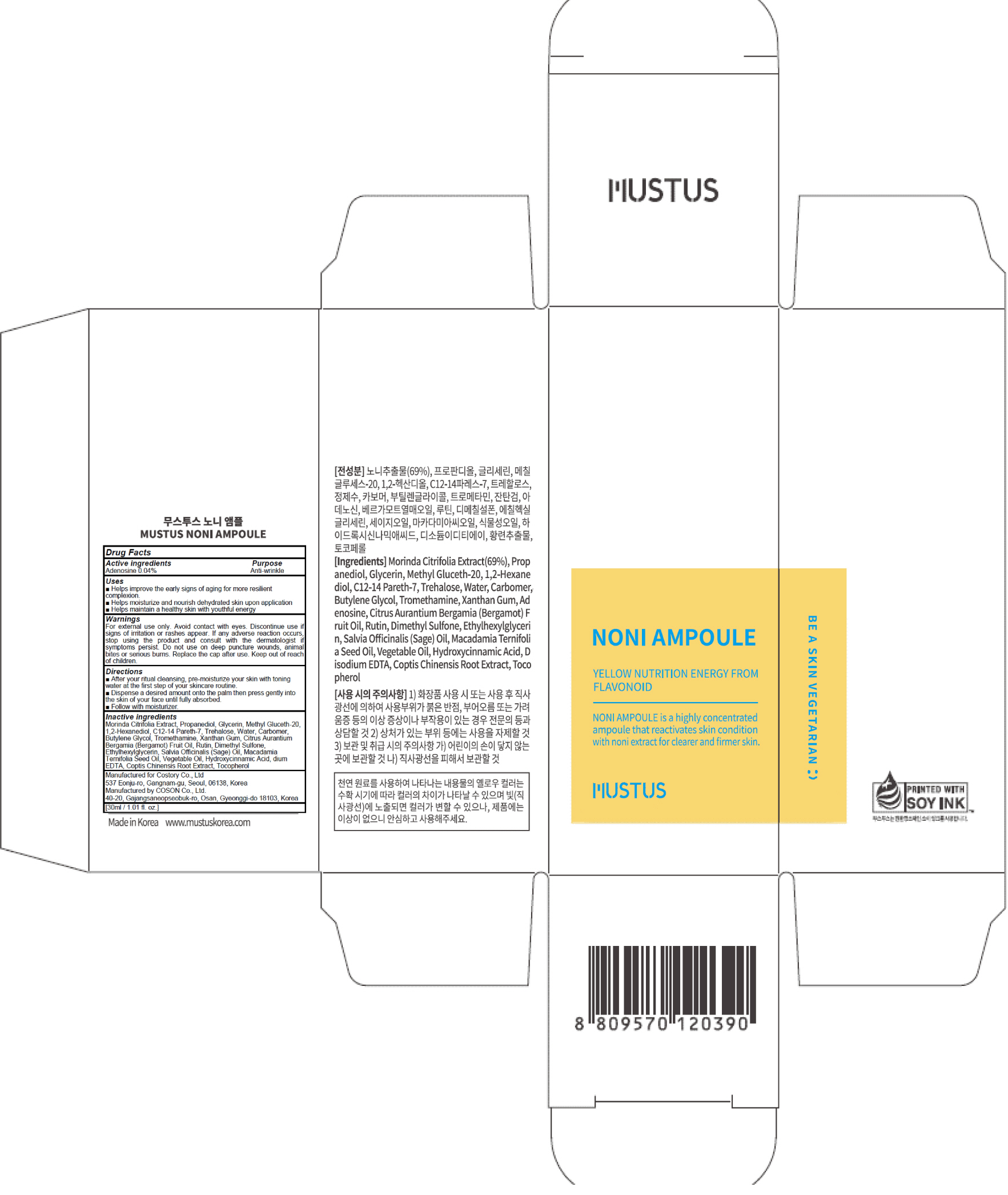 DRUG LABEL: MUSTUS NONI AMPOULE
NDC: 73020-030 | Form: LIQUID
Manufacturer: Costory Co., Ltd
Category: otc | Type: HUMAN OTC DRUG LABEL
Date: 20190509

ACTIVE INGREDIENTS: Adenosine 0.012 g/30 mL
INACTIVE INGREDIENTS: Propanediol; Glycerin

ACTIVE INGREDIENT

Active ingredients: Adenosine 0.04%

INACTIVE INGREDIENT

Inactive ingredients:

Morinda Citrifolia Extract, Propanediol, Glycerin, Methyl Gluceth-20, 1,2-Hexanediol, C12-14 Pareth-7, Trehalose, Water, Carbomer, Butylene Glycol, Tromethamine, Xanthan Gum, Citrus Aurantium Bergamia (Bergamot) Fruit Oil, Rutin, Dimethyl Sulfone, Ethylhexylglycerin, Salvia Officinalis (Sage) Oil, Macadamia Ternifolia Seed Oil, Vegetable Oil, Hydroxycinnamic Acid, dium EDTA, Coptis Chinensis Root Extract, Tocopherol

PURPOSE

Purpose: Anti-wrinkle

WARNINGS

For external use only. Avoid contact with eyes. Discontinue use if signs of irritation or rashes appear. If any adverse reaction occurs, stop using the product and consult with the dermatologist if symptoms persist. Do not use on deep puncture wounds, animal bites or serious burns. Do not reuse the sheet once used. Keep out of reach of children.

KEEP OUT OF REACH OF CHILDREN

Uses

■ Helps improve the early signs of aging for more resilient complexion.
■ Helps moisturize and nourish dehydrated skin upon application
■ Helps maintain a healthy skin with youthful energy

Directions

■ After your ritual cleansing, pre-moisturize your skin with toning water at the first step of your skincare routine.
■ Dispense a desired amount onto the palm then press gently into the skin of your face until fully absorbed.
■ Follow with moisturizer.